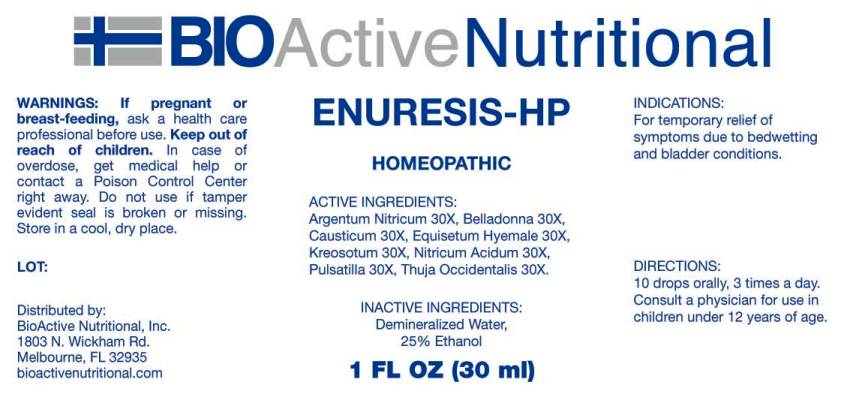 DRUG LABEL: Enuresis
NDC: 43857-0413 | Form: LIQUID
Manufacturer: BioActive Nutritional, Inc.
Category: homeopathic | Type: HUMAN OTC DRUG LABEL
Date: 20160907

ACTIVE INGREDIENTS: SILVER NITRATE 30 [hp_X]/1 mL; ATROPA BELLADONNA 30 [hp_X]/1 mL; CAUSTICUM 30 [hp_X]/1 mL; EQUISETUM HYEMALE 30 [hp_X]/1 mL; WOOD CREOSOTE 30 [hp_X]/1 mL; NITRIC ACID 30 [hp_X]/1 mL; PULSATILLA VULGARIS 30 [hp_X]/1 mL; THUJA OCCIDENTALIS LEAFY TWIG 30 [hp_X]/1 mL
INACTIVE INGREDIENTS: WATER; ALCOHOL

Drug Facts:

ACTIVE INGREDIENTS:

Argentum Nitricum 30X, Belladonna 30X, Causticum 30X, Equisetum Hyemale 30X, Kreosotum 30X, Nitricum Acidum 30X, Pulsatilla (Vulgaris) 30X, Thuja Occidentalis 30X.

INDICATIONS:

For temporary relief of symptoms due to bedwetting and bladder conditions.

WARNINGS:

If pregnant or breast-feeding, ask a health care professional before use.

Keep out of reach of children. In case of overdose, get medical help or contact a Poison Control Center right away.

Do not use if tamper evident seal is broken or missing.

Store in cool, dry place.

Keep out of reach of children. In case of overdose, get medical help or contact a Poison Control Center right away.

DIRECTIONS:

10 drops orally, 3 times a day. Consult a physician for use in children under 12 years of age.

INDICATIONS:

For temporary relief of symptoms due to bedwetting and bladder conditions.

INACTIVE INGREDIENTS:

Demineralized water, 25% Ethanol

QUESTIONS:

Distributed by:
BioActive Nutritional, Inc.
1803 N. Wickham Rd.
Melbourne, FL 32935
bioactivenutritional.com

PACKAGE LABEL DISPLAY:

BIOActive Nutritional

ENURESIS-HP

HOMEOPATHIC

1 FL OZ (30 ml)